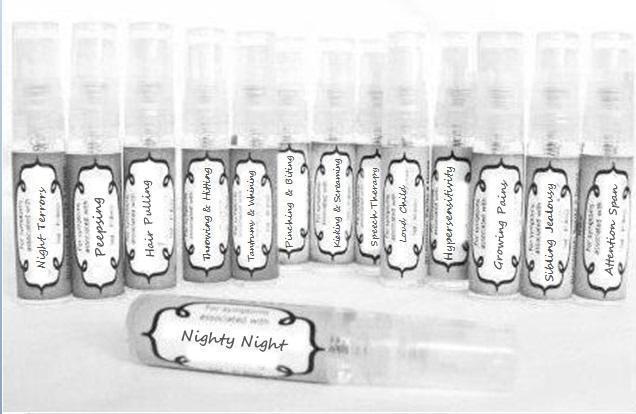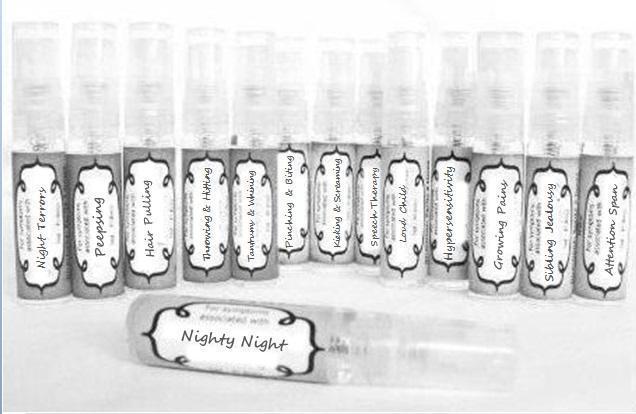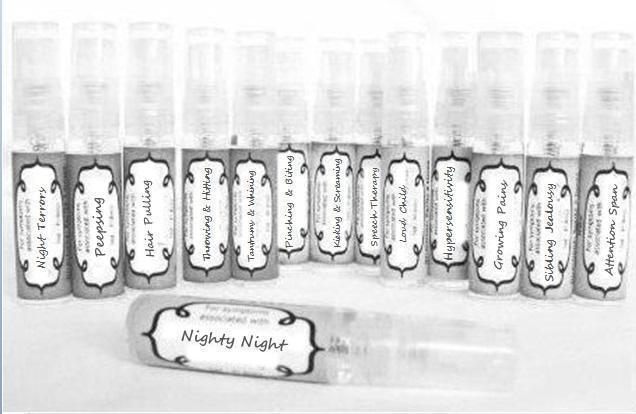 DRUG LABEL: Tantrums and Whining
NDC: 59667-0075 | Form: SPRAY
Manufacturer: Home Sweet Homeopathics
Category: homeopathic | Type: HUMAN OTC DRUG LABEL
Date: 20130802

ACTIVE INGREDIENTS: ARSENIC ACID 30 [hp_C]/30 [hp_C]; ATROPA BELLADONNA 30 [hp_C]/30 [hp_C]; TRIBASIC CALCIUM PHOSPHATE 30 [hp_C]/30 [hp_C]; MATRICARIA RECUTITA 30 [hp_C]/30 [hp_C]; ARTEMISIA CINA PRE-FLOWERING TOP 30 [hp_C]/30 [hp_C]; STRYCHNOS IGNATII SEED 30 [hp_C]/30 [hp_C]; PULSATILLA VULGARIS 30 [hp_C]/30 [hp_C]; SODIUM CHLORIDE 30 [hp_C]/30 [hp_C]; STRYCHNOS NUX-VOMICA SEED 30 [hp_C]/30 [hp_C]; THUJA OCCIDENTALIS LEAFY TWIG 30 [hp_C]/30 [hp_C]
INACTIVE INGREDIENTS: WATER; ALCOHOL

PURPOSE

For symptoms associated with

To be used according to label indications.

Directions:

Spritz 1 time under the tongue 3 x per day until improvement is seen, dose once each time symptoms return.

Keep out of reach of children.

WARNINGS

If no improvement is seen after 7 days or new symptoms develop, discontinue use.

Active ingredients:

listed for each remedy.

Inactive Ingredients:

In reverse osmosis water with less than 1% alcohol.